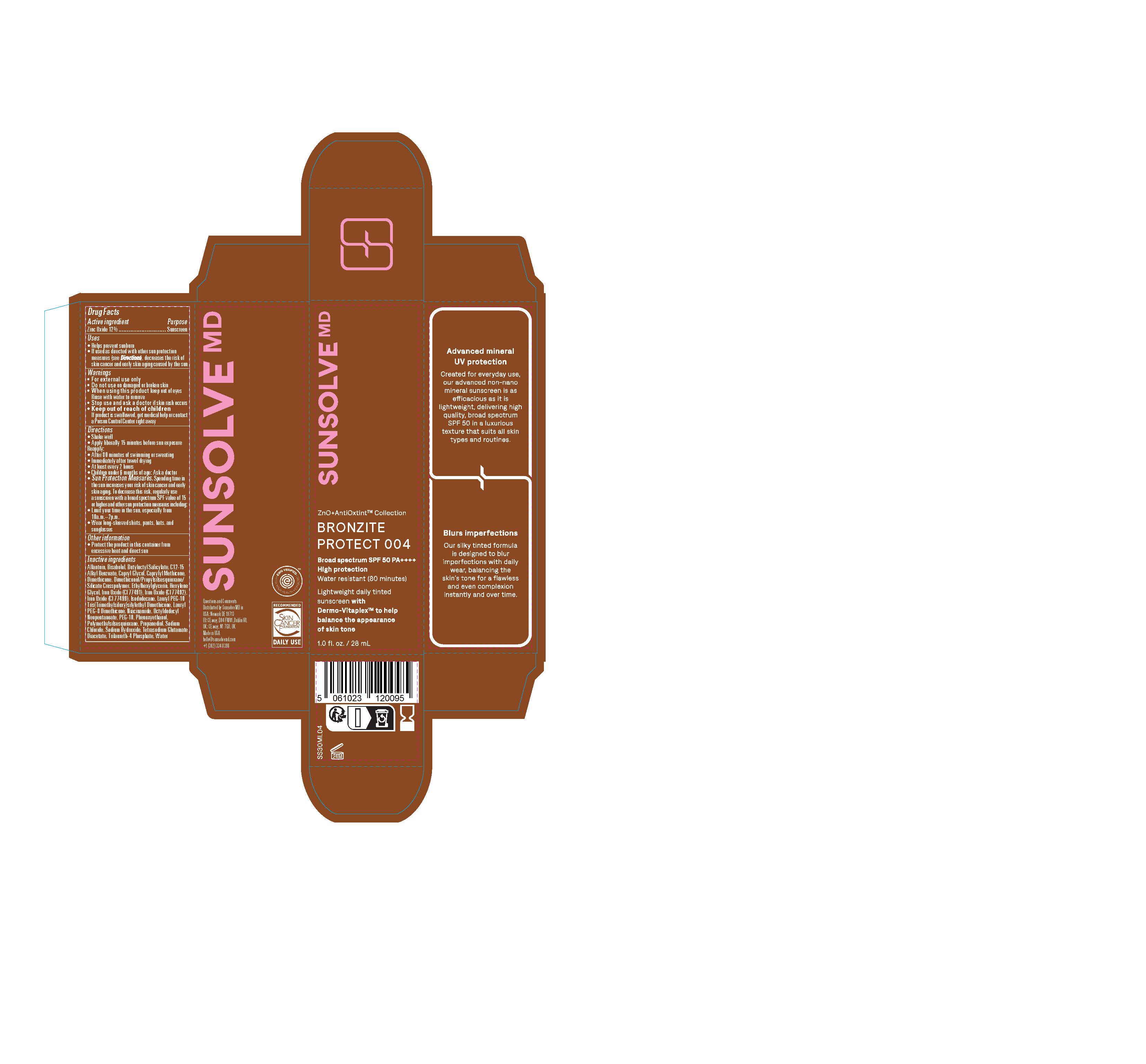 DRUG LABEL: Sunsolve MD Mineral Shade Bronzite 004
NDC: 84878-404 | Form: LOTION
Manufacturer: Sunsolve MD Inc
Category: otc | Type: HUMAN OTC DRUG LABEL
Date: 20251114

ACTIVE INGREDIENTS: ZINC OXIDE 132 mg/1 mL
INACTIVE INGREDIENTS: LAURYL PEG-8 DIMETHICONE (300 CPS); FERRIC OXIDE YELLOW; ALKYL (C12-15) BENZOATE; FERROSOFERRIC OXIDE; POLYETHYLENE GLYCOL 500; ALLANTOIN; SODIUM HYDROXIDE; WATER; NIACINAMIDE; ETHYLHEXYLGLYCERIN; HEXYLENE GLYCOL; DIMETHICONOL/PROPYLSILSESQUIOXANE/SILICATE CROSSPOLYMER (450000000 MW); PROPANEDIOL; TETRASODIUM GLUTAMATE DIACETATE; SODIUM CHLORIDE; PHENOXYETHANOL; TOCOPHEROL; DIMETHICONE; TRILAURETH-4 PHOSPHATE; BUTYLOCTYL SALICYLATE; OCTYLDODECYL NEOPENTANOATE; ISODODECANE; .ALPHA.-BISABOLOL, (+)-; POLYMETHYLSILSESQUIOXANE (4.5 MICRONS); FERRIC OXIDE RED

Sunsolve MD Mineral Shade Bronzite 004